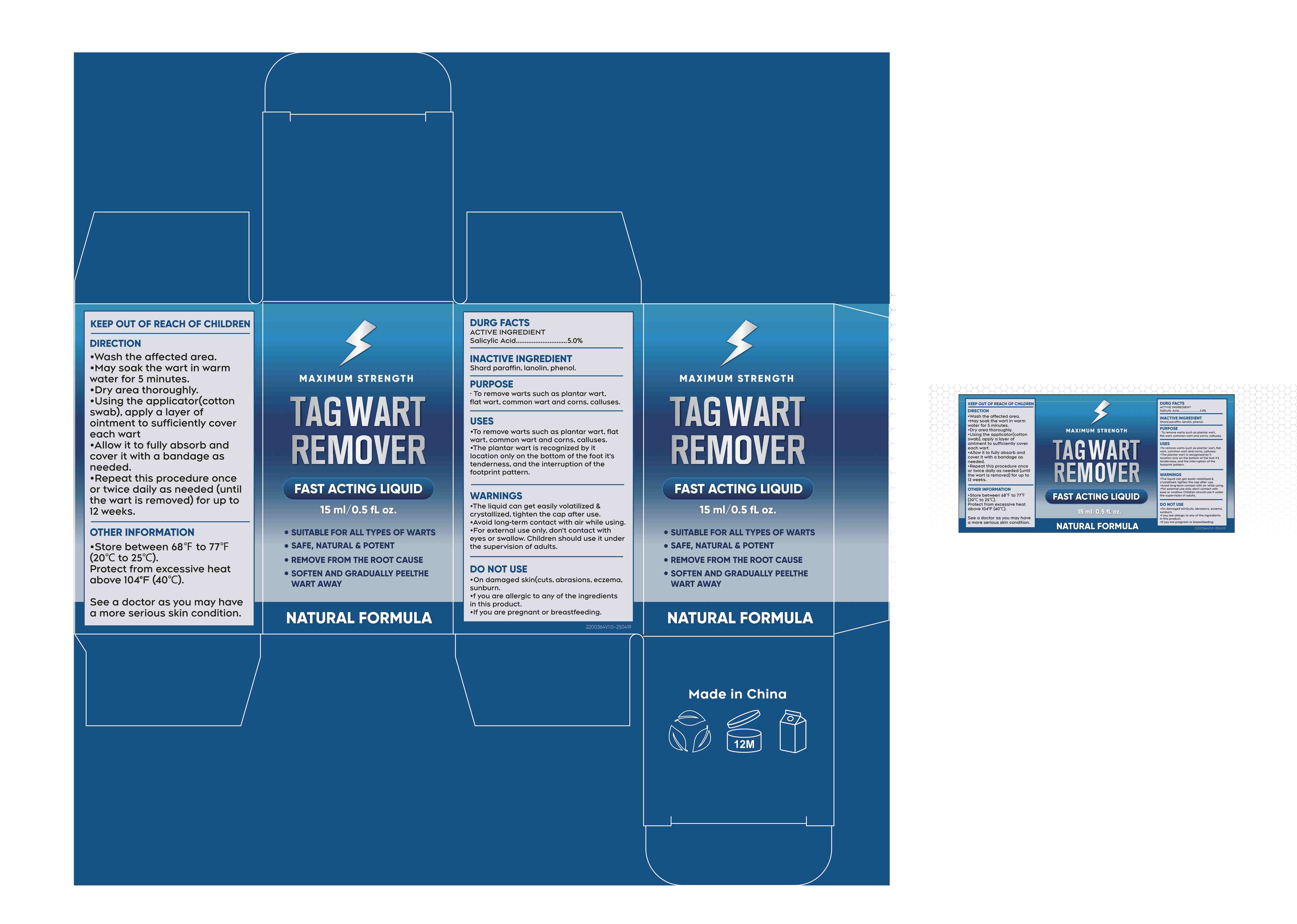 DRUG LABEL: TAG WART REMOVER
NDC: 84023-118 | Form: LIQUID
Manufacturer: Shenzhen Yangan Technology Co., Ltd.
Category: otc | Type: HUMAN OTC DRUG LABEL
Date: 20250421

ACTIVE INGREDIENTS: SALICYLIC ACID 5 mg/100 mL
INACTIVE INGREDIENTS: PARAFFIN; LANOLIN; PHENOL

ACTIVE INGREDIENT

Salicyic Acid......................5.0%

PURPOSE

To remove warts such as plantar wart, flat wart, common wart and corns, calluses.

INDICATIONS AND USAGE

·To remove warts such as plantarvart.flat wart,common wart and corns,calluses.

·The plantar wart is recognized by it location only on the bottom of the foot it’s tenderness，and the interruption of the footprint pattern

KEEP OUT OF REACH OF CHILDREN

DO NOT USE

·On damaged skin cuts, abrasions, eczema sunburn.

·f you are allergic to any of the ingredients in this product.

·lf you are pregnant or breastfeeding

DOSAGE AND ADMINISTRATION

·Wash the affected area.

·May soak the wart in warm water for 5 minutes.

·Dry area thoroughly.

·Using the applicator(cotton swab）apply a layer of ointment to sufficiently cover each wart

·Allow it to fully absorb and cover it with a bandage as needed.

·Repeat this procedure once or twice daily as needed (until the wart is removed)for upto12weeks.

WARNINGS

·The liquid can get easily volatilized crystallized. tighten the cap after use.

·Avoid long-term contact with air while using.

·For external use only, don’t contact with eyes or swallow. Children should use it under the supervision of adults.

INACTIVE INGREDIENT

Shard paraffin, lanolin, phenol.

OTHER SAFETY INFORMATION

Store between 68°F to 77°F（20°Cto25°C).

Protect from excessive heatabove 104°F（40°C）